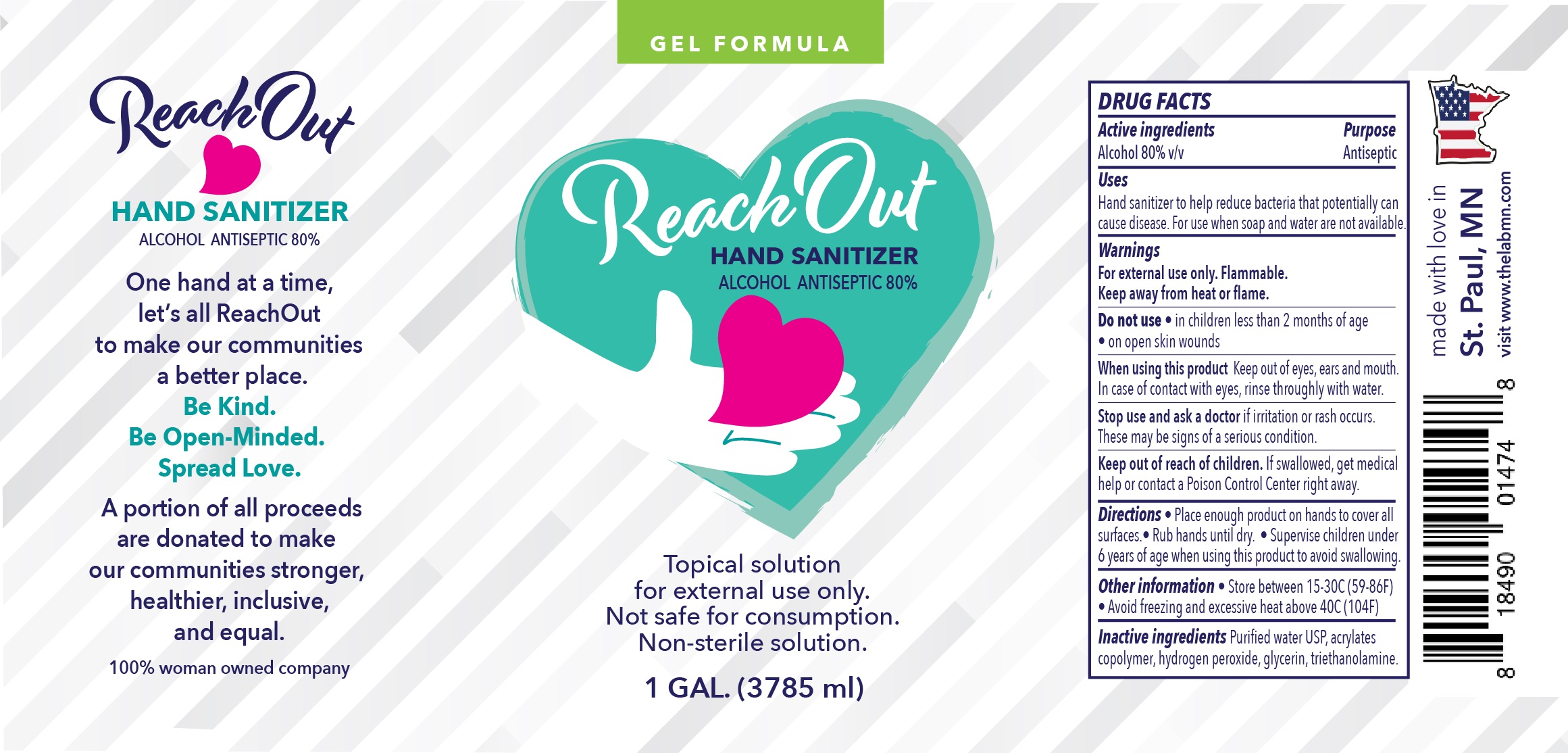 DRUG LABEL: Hand Sanitizer
NDC: 74184-001 | Form: LIQUID
Manufacturer: The Lab LLC
Category: otc | Type: HUMAN OTC DRUG LABEL
Date: 20200826

ACTIVE INGREDIENTS: ALCOHOL 80 mL/100 mL
INACTIVE INGREDIENTS: TRIETHANOLAMINE TRIS(DIHYDROGEN PHOSPHATE) 0.005 mL/100 mL; GLYCERIN 0.015 mL/100 mL; HYDROGEN PEROXIDE 0.04 mL/100 mL; WATER 19.9 mL/100 mL; PEG-10 ACRYLATE/PERFLUOROHEXYLETHYL ACRYLATE COPOLYMER 0.05 mL/100 mL

Hand Sanitizer

This is a hand sanitizer manufactured per guidance outlined in the final ruling of 21 CFR Part 310- Safety and Effectiveness of Consumer Antiseptic Rubs; Topical Antimicrobial Drug Products for Over-the-Counter Human Use. The hand sanitizer is manufactured using only the following United States Pharmacopoeia (USP) grade ingredients in the preparation of the product (percentage in final product formulation):

1. Alcohol (ethanol) (USP or Food Chemical Codex (FCC) grade) (80%, volume/volume (v/v))
2. Glycerin 98% (0.015% v/v).
3. Hydrogen peroxide 3% (0.04% v/v).
4. Sterile distilled water or boiled cold water (19.9% v/v).
5. Acrylates Copolymer (rheology modifier) (0.05% v/v).
6. Triethanolamine (pH neutralizer) (0.005% v/v).

Active Ingredient(s)

Alcohol 80% v/v. Purpose: Antiseptic

Purpose

Antiseptic, Hand Sanitizer

Uses

Hand Sanitizer to help reduce bacteria that potentially can cause disease. For use when soap and water are not available.

Warnings

For external use only. Flammable. Keep away from heat or flame

Do not use

- in children less than 2 months of age
- on open skin wounds

When using this product keep out of eyes, ears, and mouth. In case of contact with eyes, rinse thoroughly with water.
Stop use and ask a doctor if irritation or rash occurs. These may be signs of a serious condition.
Keep out of reach of children. If swallowed, get medical help or contact a Poison Control Center right away.

Stop use and ask a doctor if irritation or rash occurs. These may be signs of a serious condition.

Keep out of reach of children. If swallowed, get medical help or contact a Poison Control Center right away.

Directions

- Place enough product on hands to cover all surfaces. Rub hands until dry.
- Supervise children under 6 years of age when using this product to avoid swallowing.

Other information

- Store between 15-30C (59-86F)
- Avoid freezing and excessive heat above 40C (104F)

Inactive ingredients

Purified water USP, acrylates copolymer, hydrogen peroxide, glycerin, triethanolamine